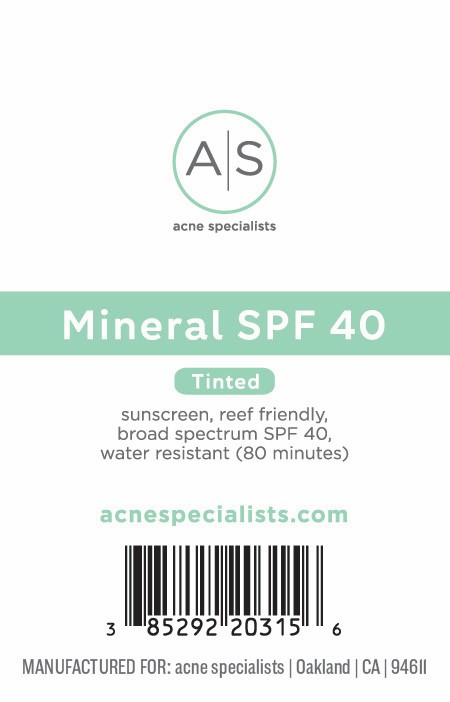 DRUG LABEL: Mineral SPF 40, Tinted
NDC: 85292-203 | Form: CREAM
Manufacturer: Acne Specialists LLC
Category: otc | Type: HUMAN OTC DRUG LABEL
Date: 20251208

ACTIVE INGREDIENTS: ZINC OXIDE 38 mg/1 g; TITANIUM DIOXIDE 80 mg/1 g
INACTIVE INGREDIENTS: ALPHA-TOCOPHEROL ACETATE; DIMETHICONE; CI 77491; HYDROGEN DIMETHICONE (20 CST); ALUMINA; DIMETHICONOL (2000 CST); DIMETHICONE/VINYL DIMETHICONE CROSSPOLYMER (SOFT PARTICLE); PEG-10 DIMETHICONE (600 CST); DIMETHICONE CROSSPOLYMER; LAURYL PEG/PPG-18/18 METHICONE; CYCLOHEXASILOXANE; TETRAHEXYLDECYL ASCORBATE; CYCLOPENTASILOXANE

Active Ingredients:

Titanium Dioxide 8% Zinc Oxide 3.8%

Purpose:

Sunscreen

Warning:

- For external use only.
- Keep out of reach of children.

Warning:

- For external use only
- Keep out of reach of children

Directions:

- Apply liberally 15 minutes before sun exposure

INACTIVE INGREDIENT

Alumina, Cyclohexasiloxane, Cyclopentasiloxane, Dimethicone, Dimethicone Crosspolymer, Dimethicone/Vinyl Dimethicone Crosspolymer, Dimethiconol, Iron Oxide (CI 77491), Lauryl PEG/PPG-18/18 Methicone, Hydrogen Dimethicone, PEG-10 Dimethicone, Tetrahexyldecyl Ascorbate, Tocopheryl Acetate

Cu

OTHER SAFETY INFORMATION

SAMPLE NOT FOR RESALE

Warning:

Keep out of reach of children